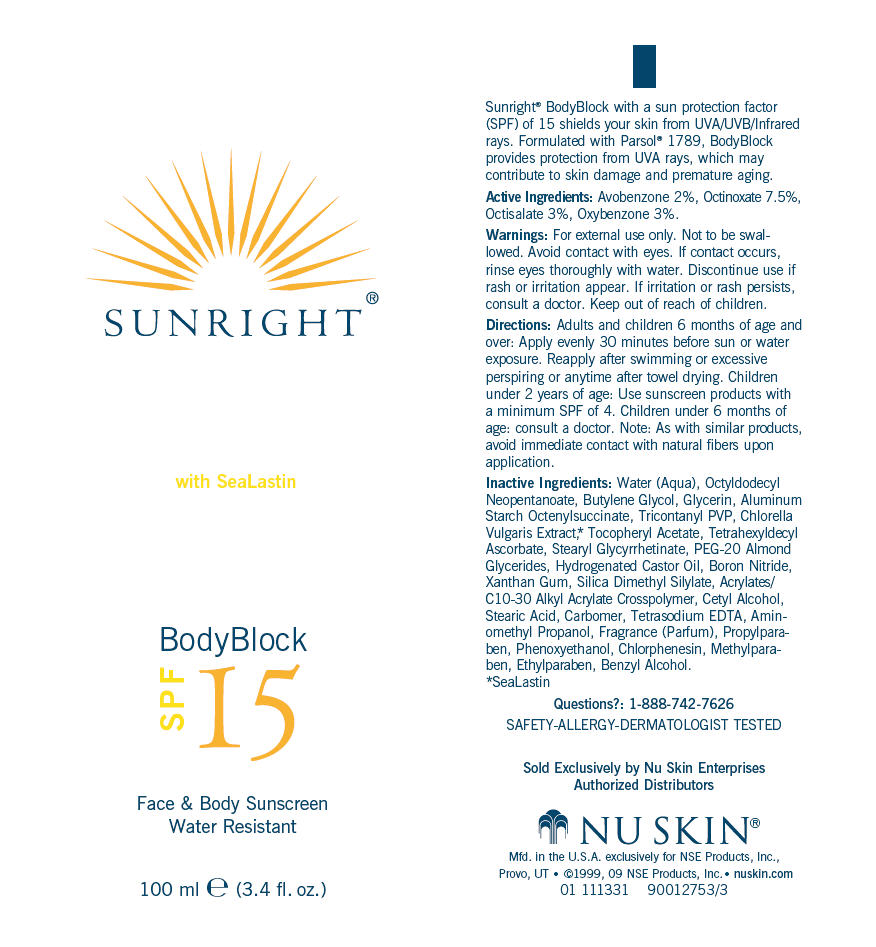 DRUG LABEL: Sunright BodyBlock SPF15
NDC: 62839-1133 | Form: LOTION
Manufacturer: NSE Products, Inc.
Category: otc | Type: HUMAN OTC DRUG LABEL
Date: 20100813

ACTIVE INGREDIENTS: Avobenzone 20 g/1000 mL; Octinoxate 75 g/1000 mL; Octisalate 30 g/1000 mL; Oxybenzone 30 g/1000 mL
INACTIVE INGREDIENTS: Water; Octyldodecyl Neopentanoate; Butylene Glycol; Glycerin; Aluminum Starch Octenylsuccinate; Chlorella Vulgaris; Tetrahexyldecyl Ascorbate; Hydrogenated Castor Oil; Boron Nitride; Xanthan Gum; Cetyl Alcohol; Stearic Acid; Edetate Sodium; Aminomethylpropanol; Propylparaben; Phenoxyethanol; Chlorphenesin; Methylparaben; Ethylparaben; Benzyl Alcohol

SUNRIGHT®
BodyBlock
SPF 15

Active Ingredients

Avobenzone 2%, Octinoxate 7.5%, Octisalate 3%, Oxybenzone 3%.

Warnings

For external use only.

WHEN USING

Not to be swallowed. Avoid contact with eyes. If contact occurs, rinse eyes thoroughly with water.

STOP USE

Discontinue use if rash or irritation appear. If irritation or rash persists, consult a doctor.

Keep out of reach of children.

Directions

Adults and children 6 months of age and over: Apply evenly 30 minutes before sun or water exposure. Reapply after swimming or excessive perspiring or anytime after towel drying. Children under 2 years of age: Use sunscreen products with a minimum SPF of 4. Children under 6 months of age: consult a doctor. Note: As with similar products, avoid immediate contact with natural fibers upon application.

Inactive Ingredients

Water (Aqua), Octyldodecyl Neopentanoate, Butylene Glycol, Glycerin, Aluminum Starch Octenylsuccinate, Tricontanyl PVP, Chlorella Vulgaris Extract, [SeaLastin] Tocopheryl Acetate, Tetrahexyldecyl Ascorbate, Stearyl Glycyrrhetinate, PEG-20 Almond Glycerides, Hydrogenated Castor Oil, Boron Nitride, Xanthan Gum, Silica Dimethyl Silylate, Acrylates/C10-30 Alkyl Acrylate Crosspolymer, Cetyl Alcohol, Stearic Acid, Carbomer, Tetrasodium EDTA, Aminomethyl Propanol, Fragrance (Parfum), Propylparaben, Phenoxyethanol, Chlorphenesin, Methylparaben, Ethylparaben, Benzyl Alcohol.

Questions?

1-888-742-7626

PRINCIPAL DISPLAY PANEL - 100 ml Carton

SUNRIGHT®

with SeaLastin

BodyBlock
SPF 15

Face & Body Sunscreen
Water Resistant

100 ml e (3.4 fl. oz.)